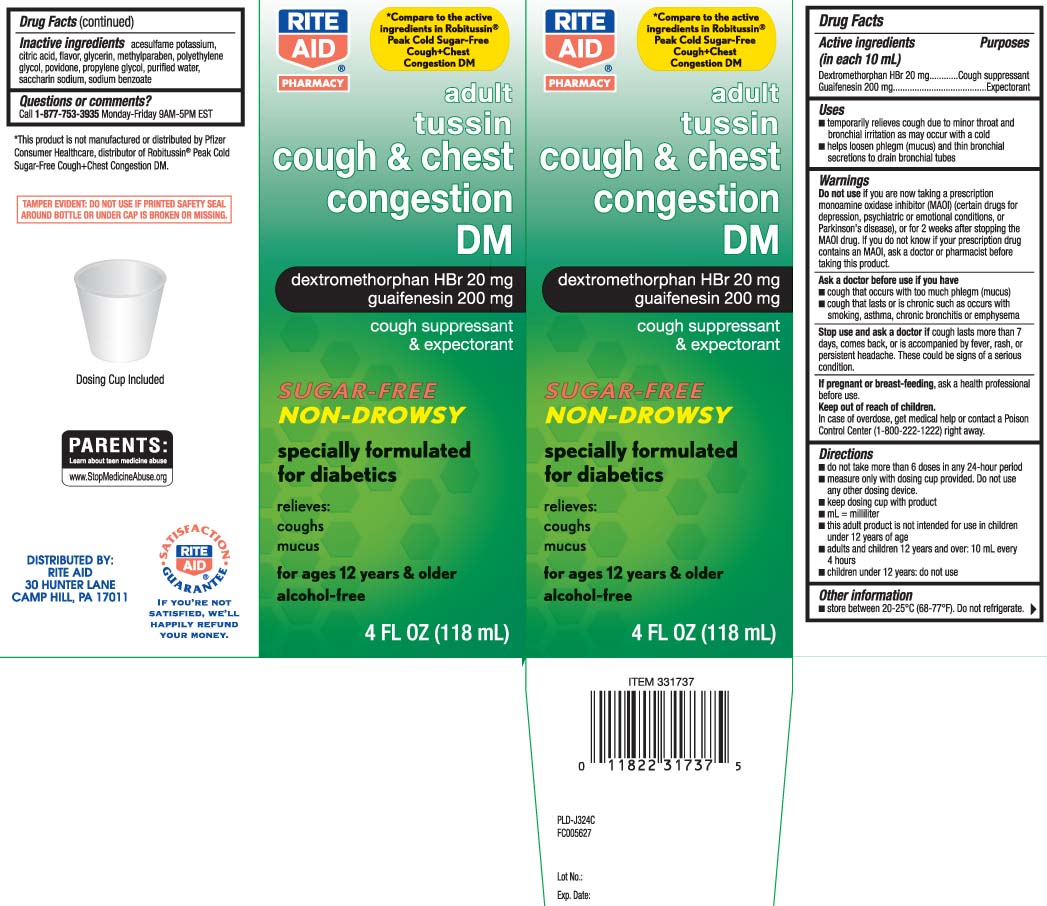 DRUG LABEL: Tussin Cough DM
NDC: 11822-3840 | Form: LIQUID
Manufacturer: Rite Aid Corporation
Category: otc | Type: HUMAN OTC DRUG LABEL
Date: 20260102

ACTIVE INGREDIENTS: DEXTROMETHORPHAN HYDROBROMIDE 20 mg/10 mL; GUAIFENESIN 200 mg/10 mL
INACTIVE INGREDIENTS: ACESULFAME POTASSIUM; ANHYDROUS CITRIC ACID; GLYCERIN; METHYLPARABEN; POLYETHYLENE GLYCOL, UNSPECIFIED; POVIDONE; PROPYLENE GLYCOL; WATER; SACCHARIN SODIUM; SODIUM BENZOATE

Drug Facts

Active ingredients (in each 10 mL)

Dextromethorphan HBr 20 mg

Guaifenesin 200 mg

Purposes

Cough suppressant

Expectorant

Uses

- temporarily relieves cough due to minor throat and bronchial irritation as may occur with a cold
- helps loosen phlegm (mucus) and thin bronchial secretions to drain bronchial tubes

Warnings

Do not use

if you are now taking a prescription monoamine oxidase inhibitor (MAOI) (certain drugs for depression, psychiatric or emotional conditions, or Parkinson’s disease), or for 2 weeks after stopping the MAOI drug. If you do not know if your prescription drug contains an MAOI, ask a doctor or pharmacist before taking this product.

Ask a doctor before use if you have

- cough that occurs with too much phlegm (mucus)
- cough that lasts or is chronic such as occurs with smoking, asthma, chronic bronchitis, or emphysema

Stop use and ask a doctor if

cough lasts more than 7 days, comes back, or is accompanied by fever, rash, or persistent headache. These could be signs of a serious condition.

If pregnant or breast-feeding,

ask a health professional before use.

keep out of reach of children.

In case of overdose, get medical help or contact a Poison Control Center (1-800-222-1222) right away.

Directions

- do not take more than 6 doses in any 24-hour period
- measure only with dosing cup provided. Do not use any other dosing device
- keep dosing cup with product
- mL = milliliter
- this adults product is not intended for use in children under 12 years of age
- adults and children 12 years and over: 10 mL every 4 hours
- children under 12 years: do not use

Other information

- store between 20-25ºC (68-77º). Do not refrigerate.

Inactive ingredients

acesulfame potassium, citric acid, flavors, glycerin, methylparaben, polyethylene glycol, povidone, propylene glycol, purified water, saccharin sodium, sodium benzoate

Questions or comments?

Call 1-877-753-3935 Monday-Friday 9AM-5PM EST

Principal Display Panel

*Compare to the active ingredients in Robitussin® Peak Cold Sugar-Free Cough + Chest Congestion DM

adult

tussin

cough & chest Congestion DM

dextromethorphan HBr 20 mg

guaifenesin 200 mg

cough suppressant &

expectorant

SUGAR-FREE

NON-DROWSY

specially formulated for diabetics

relieves:

coughs

mucus

for ages 12 years & older

alcohol-free

FL OZ (mL)

Dosing Cup Included

*This product is not manufactured or distributed by Pfizer Consumer Healthcare, distributors of Robitussin® Peak Cold Sugar-Free Cough+Chest Congestion DM.

TAMPER EVIDENT: DO NOT USE IF PRINTED SAFETY SEAL AROUND BOTTLE OR UNDER CAP IS BROKEN OR MISSING.

DISTRIBUTED BY:

RITE AID

30 HUNTER LANE

CAMP HILL, PA 17011

Package Label

RITE AID PHARMACY Adult Tussin Cough & Chest Congestion DM